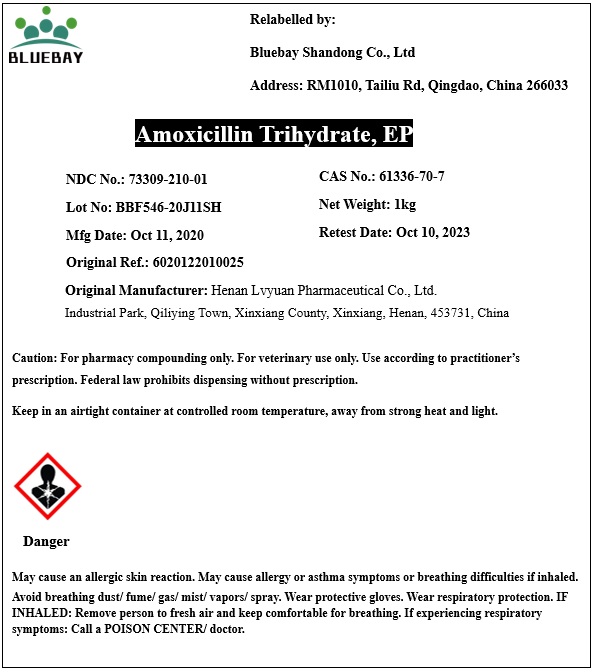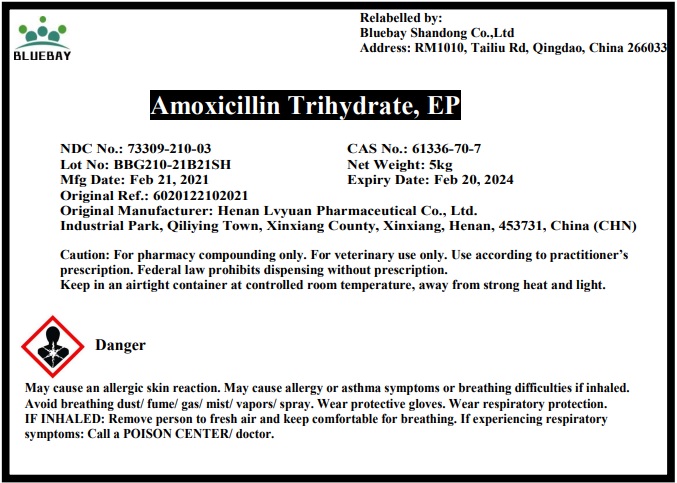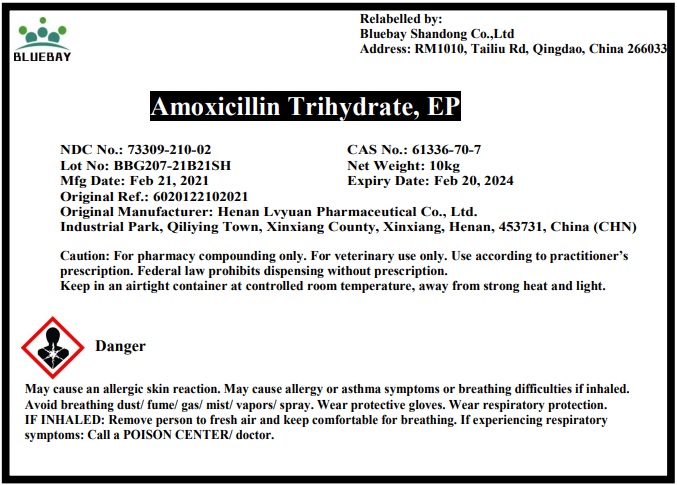 DRUG LABEL: Amoxicillin Trihydrate
NDC: 73309-210 | Form: POWDER
Manufacturer: BLUEBAY SHANDONG CO.,LTD
Category: other | Type: BULK INGREDIENT
Date: 20210416

ACTIVE INGREDIENTS: AMOXICILLIN 1 kg/1 kg

Amoxicillin Trihydrate